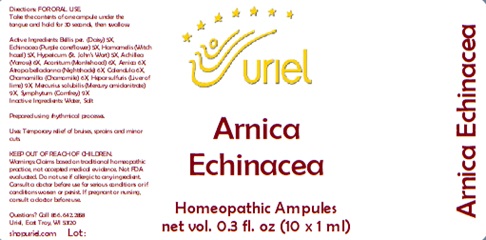 DRUG LABEL: Arnica Echinacea
NDC: 48951-1141 | Form: LIQUID
Manufacturer: Uriel Pharmacy Inc.
Category: homeopathic | Type: HUMAN OTC DRUG LABEL
Date: 20241122

ACTIVE INGREDIENTS: BELLIS PERENNIS 5 [hp_X]/1 mL; ECHINACEA, UNSPECIFIED 5 [hp_X]/1 mL; HAMAMELIS VIRGINIANA LEAF 5 [hp_X]/1 mL; ST. JOHN'S WORT 5 [hp_X]/1 mL; ACHILLEA MILLEFOLIUM 6 [hp_X]/1 mL; ACONITUM NAPELLUS 6 [hp_X]/1 mL; ARNICA MONTANA 6 [hp_X]/1 mL; ATROPA BELLADONNA 6 [hp_X]/1 mL; CALENDULA OFFICINALIS FLOWERING TOP 6 [hp_X]/1 mL; MATRICARIA RECUTITA 6 [hp_X]/1 mL; CALCIUM SULFIDE 9 [hp_X]/1 mL; MERCURIUS SOLUBILIS 9 [hp_X]/1 mL; COMFREY ROOT 9 [hp_X]/1 mL
INACTIVE INGREDIENTS: WATER; SODIUM CHLORIDE

Arnica Echinacea

INDICATIONS AND USAGE

Directions: FOR ORAL USE.

DOSAGE AND ADMINISTRATION

Take the contents of one ampule under the tongue and hold for 30 seconds, then swallow.

ACTIVE INGREDIENT

Active Ingredients: Bellis per. ex herba (Daisy) 5X, Echinacea (Purpleconeflower) 5X, Hamamelis (Witch hazel) 5X, Hypericum (St. Johns Wort) 5X, Achillea (Yarrow) 6X, Aconitum (Monkshood) 6X, Arnica (Arnica e pl. tota) 6X, Atropa belladonna (Nightshade) 6X, Calendula (Calendula ex herba) 6X, Chamomilla (Chamomile) 6X, Hepar sulfuris (Liver of Lime) 9X, Symphytum (Comfrey) 9X, Mercurius solubilis (Mercury amidonitrate) 9X

Inactive Ingredients: Water, Salt

Prepared using rhythmiocal processes.

PURPOSE

Uses: Temporary relief of bruises, sprains and minor cuts.

KEEP OUT OF REACH OF CHILDREN.

WARNINGS

Warnings: Claims based on traditional homeopathic practice, not accepted medical evidence. Not FDA evaluated. Do not use if allergic to any ingredient. Consult a doctor before use for serious conditions or if conditions worsen or persist. If pregnant or nursing, consult a doctor before use.

Questions? Call 866.642.2858
Uriel, East Troy, WI 53120
shopuriel.com Lot: